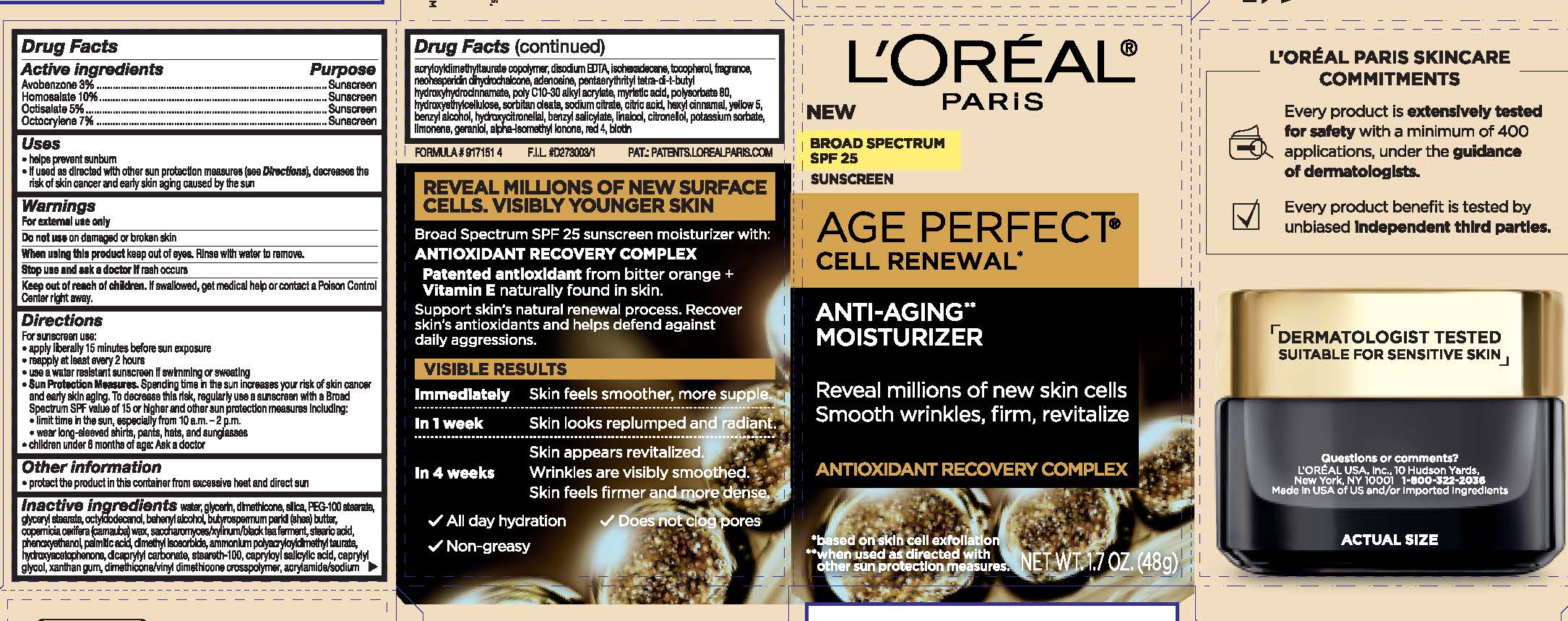 DRUG LABEL: LOreal Paris Age Perfect Cell Renewal Day Moisturizer Broad Spectrum SPF 25 Sunscreen
NDC: 49967-036 | Form: CREAM
Manufacturer: L'Oreal USA Products Inc
Category: otc | Type: HUMAN OTC DRUG LABEL
Date: 20231229

ACTIVE INGREDIENTS: AVOBENZONE 30 mg/1 g; HOMOSALATE 100 mg/1 g; OCTISALATE 50 mg/1 g; OCTOCRYLENE 70 mg/1 g
INACTIVE INGREDIENTS: WATER; GLYCERIN; ALCOHOL; HYDROGENATED POLYBUTENE (1300 MW); BIS-PEG-18 METHYL ETHER DIMETHYL SILANE; DIMETHICONE; CETOSTEARYL ALCOHOL; PEG-100 STEARATE; POLYETHYLENE GLYCOL 1000; PETROLATUM; SHEA BUTTER; C13-14 ISOPARAFFIN; GLYCERYL MONOSTEARATE; DIMETHICONOL (70 CST); DIMETHYL ISOSORBIDE; CETEARYL GLUCOSIDE; NEOHESPERIDIN DIHYDROCHALONE; SODIUM COCOYL GLUTAMATE; HYALURONATE SODIUM; SODIUM HYDROXIDE; CYCLODEXTRINS; ADENOSINE; MOTH BEAN; MANNITOL; EDETATE DISODIUM; SODIUM SUCCINATE ANHYDROUS; CAPRYLOYL SALICYLIC ACID; LAURETH-7; YEAST, UNSPECIFIED; XANTHAN GUM; POLYACRYLAMIDE (10000 MW); CETYL ALCOHOL; OCTYLDODECANOL; .ALPHA.-TOCOPHEROL ACETATE; SODIUM DEHYDROACETATE; PHENOXYETHANOL; FD&C RED NO. 4; FD&C YELLOW NO. 5; LINALOOL, (+/-)-; GERANIOL; LIMONENE, (+)-; HYDROXYCITRONELLAL; BENZYL ALCOHOL; BENZYL SALICYLATE

Drug Facts

Active ingredients

Avobenzone 3%

Homosalate 10%

Octisalate 5%

Octocrylene 7%

Purpose

Sunscreen

Uses

- helps prevent sunburn

-if used as directed with other sun protection measures (see Directions), decreases the risk of skin cancer and early skin aging caused by the sun

Warnings

For external use only

Do not use

on damaged or broken skin

When using this product

keep out of eyes. Rinse with water to remove.

Stop use and ask a doctor if

rash occurs

Keep out of reach of children.

If swallowed, get medical help or contact a Poison Control Center right away.

Directions

For sunscreen use:

● apply liberally 15 minutes before sun exposure

● reapply at least every 2 hours

● use a water resistant sunscreen if swimming or sweating

● Sun Protection Measures. Spending time in the sun increases your risk of skin cancer and early skin aging. To decrease this risk, regularly use a sunscreen with a Broad Spectrum SPF value of 15 or higher and other sun protection measures including:

● limit time in the sun, especially from 10 a.m. – 2 p.m.

● wear long-sleeved shirts, pants, hats, and sunglasses

● children under 6 months of age: Ask a doctor

Other information

protect the product in this container from excessive heat and direct sun

Inactive ingredients

water, glycerin, alcohol denat., hydrogenated polyisobutene, bis-PEG-18 methyl ether dimethyl silane, dimethicone, cetearyl alcohol, PEG-100 stearate, PEG-20, petrolatum, butyrospermum parkii (shea) butter, C13-14 isoparaffin, glyceryl stearate, dimethiconol, dimethyl isosorbide, cetearyl glucoside, neohesperidin dihydrochalcone, sodium cocoyl glutamate, sodium hyaluronate, sodium hydroxide, cyclodextrin, adenosine, vigna aconitifolia seed extract, mannitol, disodium EDTA, disodium succinate, hydrolyzed cicer seed extract, capryloyl salicylic acid, laureth-7, yeast extract, xanthan gum, polyacrylamide, acrylates/C10-30 alkyl acrylate crosspolymer, cetyl alcohol, octyldodecanol, tocopheryl acetate, sodium dehydroacetate, phenoxyethanol, red 4, yellow 5, linalool, geraniol, alpha-isomethyl ionone, limonene, hydroxycitronellal, cironellol, hexyl cinnamal, benzyl alcohol, benzyl salicylate, fragrance